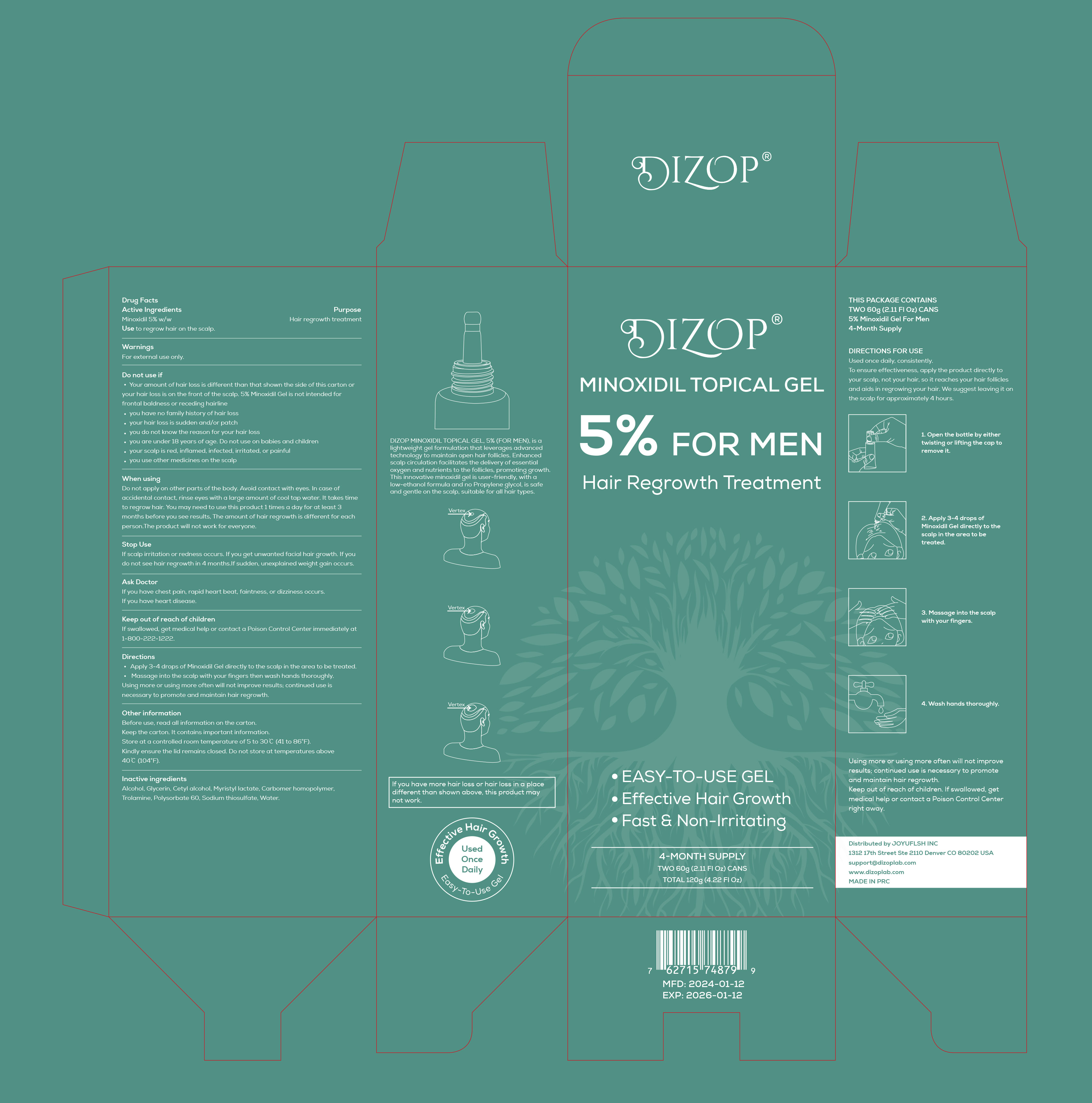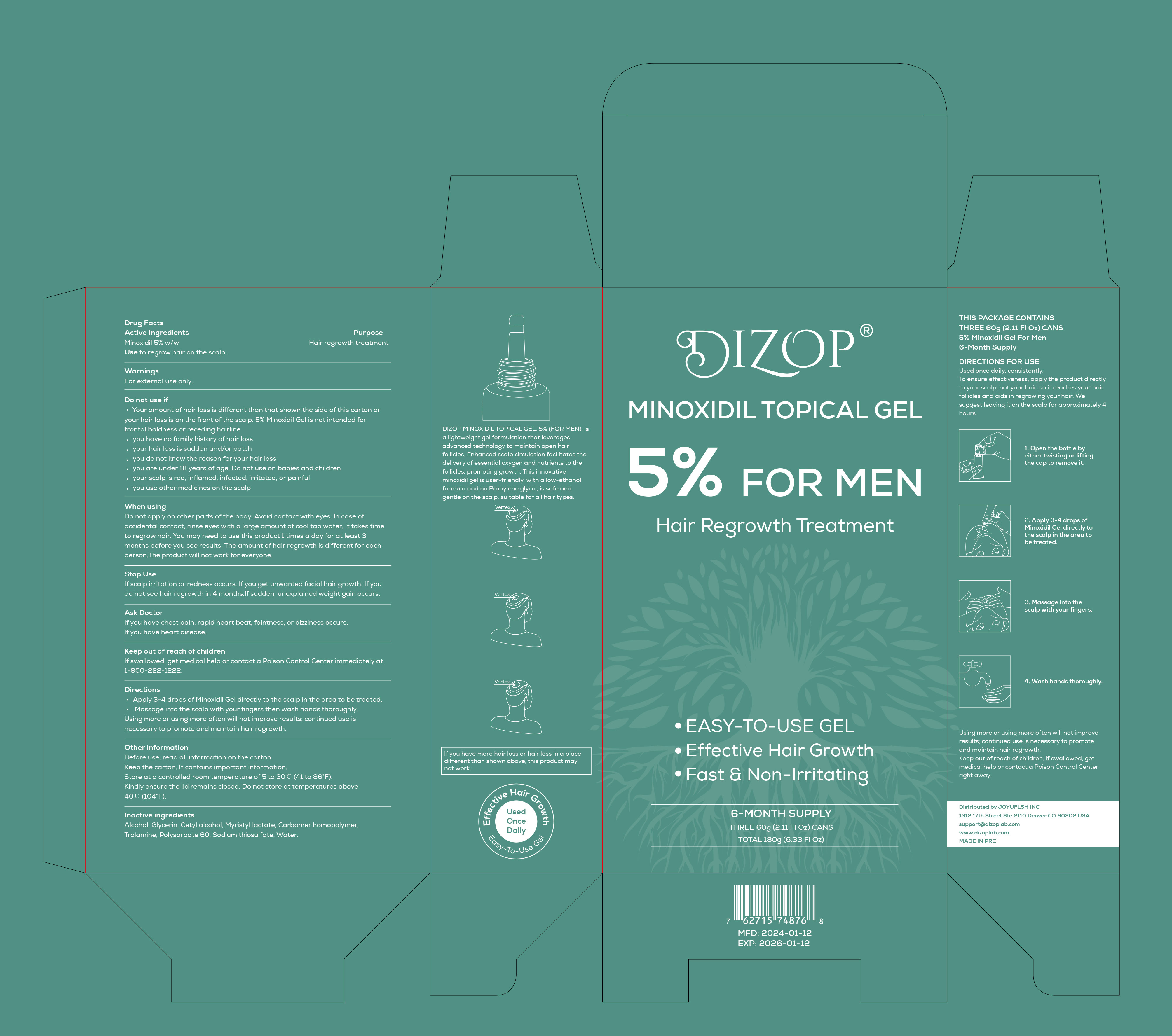 DRUG LABEL: DIZOP 5% Minoxidil Topical Gel
NDC: 83766-102 | Form: GEL
Manufacturer: Shenzhen Joyuflsh Technology Co.,Ltd.
Category: otc | Type: HUMAN OTC DRUG LABEL
Date: 20240409

ACTIVE INGREDIENTS: MINOXIDIL 5 g/100 g
INACTIVE INGREDIENTS: CARBOMER HOMOPOLYMER, UNSPECIFIED TYPE; WATER; TROLAMINE; GLYCERIN; CETYL ALCOHOL; SODIUM THIOSULFATE; MYRISTYL LACTATE; ALCOHOL; POLYSORBATE 60

DIZOP 5% Minoxidil Topical Gel

DIZOP 5% Minoxidil Topical Gel

ACTIVE INGREDIENT

Minoxidil 5%

PURPOSE

Hair regrowth treatment

INDICATIONS AND USAGE

Apply 3-4 drops of Minoxidil Gel directly to the scalp in the area to be treated.
Massage into the scalp with your fingers then wash hands thoroughly.
Using more or using more often will not improve results; continued use is necessary to promote and maintain hair regrowth.

WARNINGS

For external use only.

DO NOT USE

Your amount of hair loss is different than that shown the side of this carton or your hair loss is on the front of the scalp. 5% Minoxidil Gel is not intended for frontal baldness or receding hairline.
you have no family history of hair loss.
your hair loss is sudden and/or patch.
you do not know the reason for your hair loss.
you are under 18 years of age. Do not use on babies and children.
your scalp is red, inflamed, infected, irritated, or painful.
you use other medicines on the scalp.

WHEN USING

Do not apply on other parts of the body. Avoid contact with eyes. In case of accidental contact, rinse eyes with a large amount of cool tap water. lt takes time to regrow hair. You may need to use this product 1 times a day for at least 3 months before you see results, The amount of hair regrowth is different for each person.The product will not work for everyone.

STOP USE

lf scalp irritation or redness occurs. lf you get unwanted facial hair growth. lf you do not see hair regrowth in 4 months.lf sudden, unexplained weight gain occurs.

KEEP OUT OF REACH OF CHILDREN

lf swallowed, get medical help or contact a Poison Control Center immediately at 1-800-222-1222

DOSAGE AND ADMINISTRATION

Apply 3-4 drops of Minoxidil Gel directly to the scalp in the area to be treated.

Massage into the scalp with your fingers then wash hands thoroughly.

Using more or using more often will not improve results; continued use is necessary to promote and maintain hair regrowth.

STORAGE AND HANDLING

Before use, read all information on the carton.
Keep the carton. It contains important information.
Store at a controlled room temperature of 5 to 30 C (41 to 86°F).
Kindly ensure the lid remains closed. Do not store at temperatures above 40C(104°F).

INACTIVE INGREDIENT

Minoxidil
ALCOHOL
GLYCERIN
CETYL ALCOHOL
MYRISTYL LACTATE
POLYSORBATE 60
SODIUM THIOSULFATE
CARBOMER HOMOPOLYMER
TROLAMINE
WATER